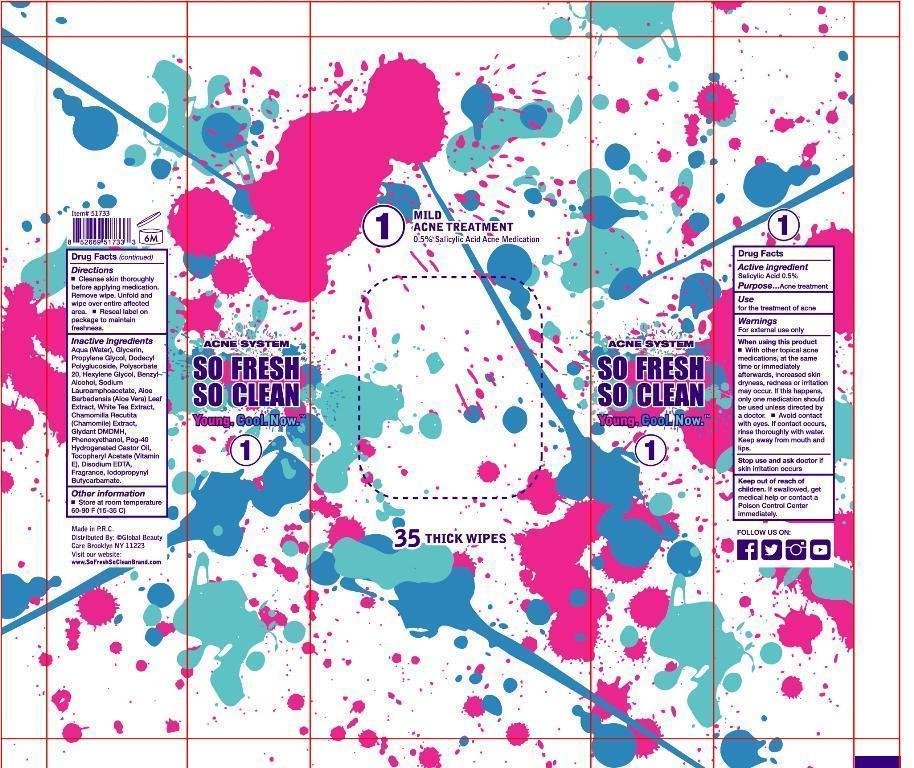 DRUG LABEL: wet wipes
NDC: 61312-004 | Form: SWAB
Manufacturer: HANGZHOU GUOGUANG TOURING COMMODITY CO., LTD.
Category: otc | Type: HUMAN OTC DRUG LABEL
Date: 20180109

ACTIVE INGREDIENTS: SALICYLIC ACID 0.5 g/100 g
INACTIVE INGREDIENTS: WATER; GLYCERIN; PROPYLENE GLYCOL; DODECYL PROPIONATE; POLYSORBATE 20; HEXYLENE GLYCOL; BENZYL ALCOHOL; SODIUM LAURAMINOPROPIONATE; ALOE VERA LEAF; TEA LEAF OIL; CHAMOMILE FLOWER OIL; DMDM HYDANTOIN; PHENOXYETHANOL; PEG-40 HYDROGENATED LANOLIN; TOCOPHERYL RETINOATE; DISODIUM EDTA-COPPER; IODOPROPYNYL BUTYLCARBAMATE

61312004

Active ingredient

salicylic acid 0.5%

Purpose

acne treatment

Use

for the treatment of acne

Warnings

for external use only
when using this product
with other topical acne medications ,at the same time or immediately afterwards ,increased skin dryness ,redness or
irritation may occur .If this happens ,only one medication should be used unless directed by a doctor.
avoid contact with eyes .if contact occurs, rinse thoroughly with water. keep away from mouth and lips.
stop use and ask doctor if skin irritation occurs.
Keep out of reach of children ,If swallowed ,get medical help or contact a Poison Control Center immediately.

Keep out of reach of children ,If swallowed ,get medical help or contact a Poison Control Center immediately.

Directions

cleanse skin thoroughly before applying medication ,remove wipe ,unfold and wipe over entire affected area.
reseal label on package to maintain freshness.

INACTIVE INGREDIENT

aqua (water),glycerin, propylene glycol , dodecyl polyglucoside, polysorbate 20,HEXYLENE GLYCOL , BENZYL ALCOHOL ,SODIUM LAURAMINOPROPIONATE ,ALOE BARBADENSIS(ALOE VERA)EXTRACT ,WHITE TEA EXTRACT ,CHAMOMILLA RECUTITA(CHAMOMILE)EXTRACT ,GLYDANT DMDM H,PHENOXYETHANOL ,PEG-40 HYDROGENATED CASTOR OIL,TOCOPHERYL ACETATE(VITAMIN E) ,DISODIUM EDTA,IODOPROPYNYL BUTYLCARBAMATE